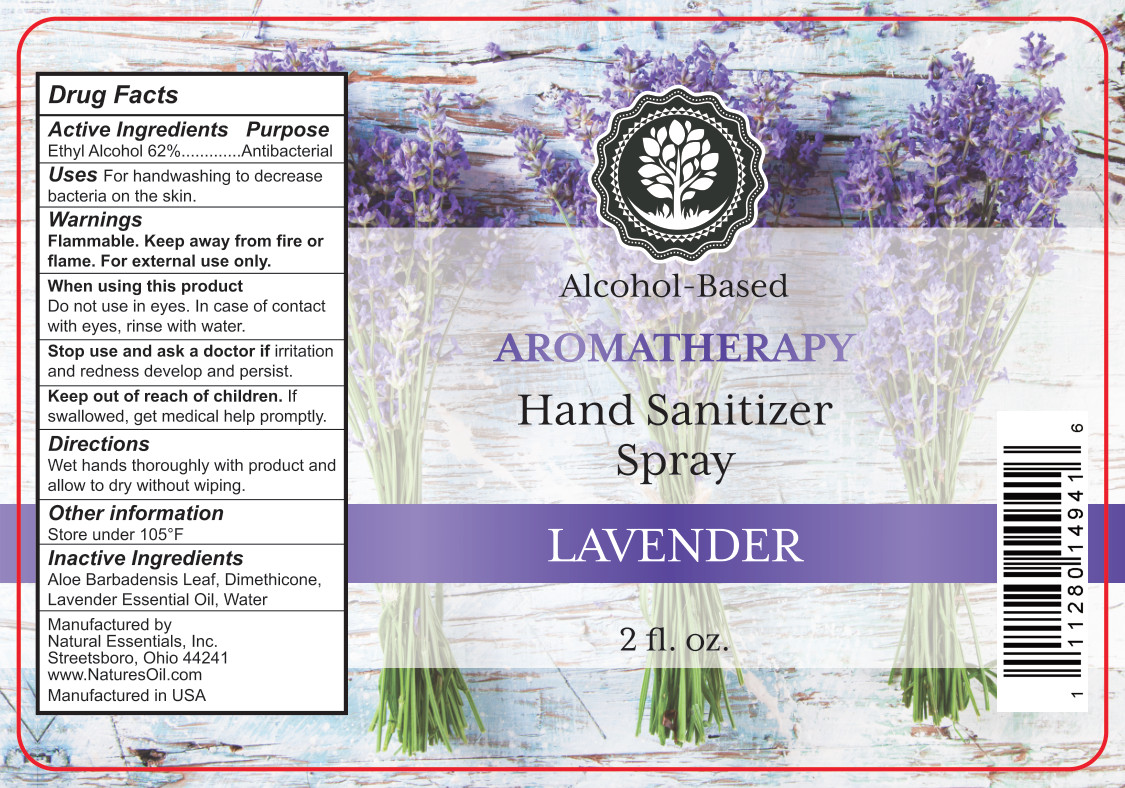 DRUG LABEL: Lavender Hand Sanitizer
NDC: 66902-548 | Form: SPRAY
Manufacturer: Natural Essentials, Inc.
Category: otc | Type: HUMAN OTC DRUG LABEL
Date: 20241031

ACTIVE INGREDIENTS: ALCOHOL 0.62 mL/1 mL
INACTIVE INGREDIENTS: ALOE VERA LEAF; DIMETHICONE; WATER; LAVENDER OIL

Active Ingredients

Ethyl Alcohol 62%

Purpose

Antibacterial

Uses

For handwashing to decrease bacteria on the skin.

Warnings

Flammable. Keep away from fire or flame. For external use only.

When using this product

Do not use in eyes. In case of contact with eyes, rinse with water.

Stop use and ask a doctor if

irritation and redness develop and persist.

Keep out of reach of children

If swallowed, get medical help promptly.

Directions

Wet hands throroughly with product and allow to dry without wiping.

Other information

Store under 105°F

Inactive ingredients

Aloe Barbadensis Leaf, Dimethicone, Lavender Essential Oil, Water

Principal Display Panel - 59 mL Bottle Label

Alchol-Based

Aromatherapy

Hand Sanitizer Spray

Lavender

2 fl. oz.